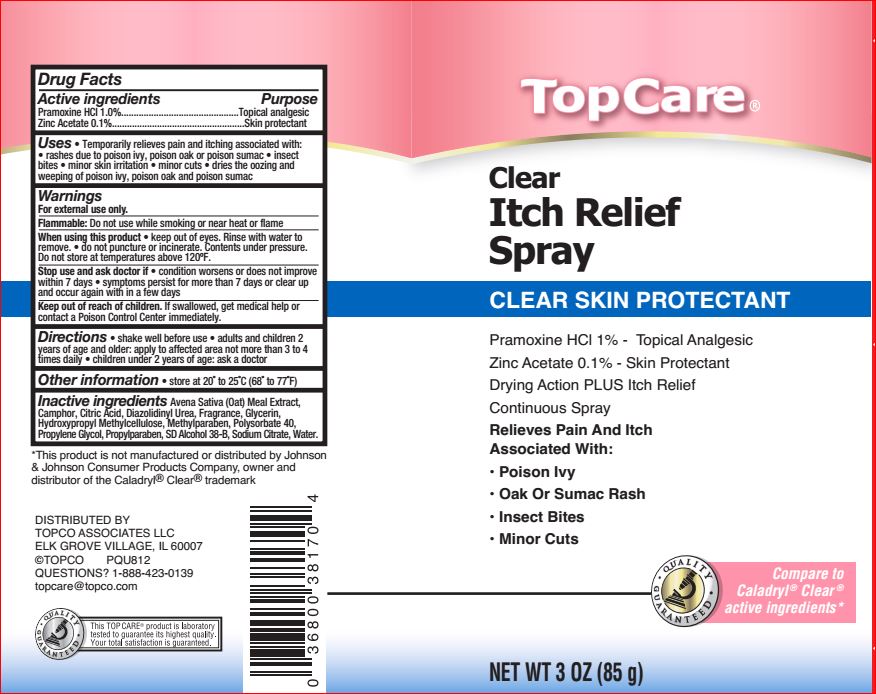 DRUG LABEL: Clear Itch Relief
NDC: 36800-874 | Form: SPRAY
Manufacturer: TopCare
Category: otc | Type: HUMAN OTC DRUG LABEL
Date: 20180625

ACTIVE INGREDIENTS: PRAMOXINE HYDROCHLORIDE 1 g/100 g; ZINC ACETATE .1 g/100 g
INACTIVE INGREDIENTS: ALCOHOL; OATMEAL; CAMPHOR (SYNTHETIC); CITRIC ACID MONOHYDRATE; DIAZOLIDINYL UREA; GLYCERIN; HYPROMELLOSE, UNSPECIFIED; METHYLPARABEN; POLYSORBATE 40; PROPYLENE GLYCOL; PROPYLPARABEN; SODIUM CITRATE; WATER

Drug Facts

Active ingredients Purpose
Pramoxine HCI 1.0%...............................................Topical analgesic
Zinc Acetate 0.1%.....................................................Skin protectant

Uses

- Temporarily relieves pain and itching asociated with:
- rashes due to poison ivy, poison oak or poison sumac.
- insect bites.
- minor skin irritation.
- minor cuts.
- dries the oozing and weeping of poison ivy, poison oak and poison sumac.

Warnings

For external use only.

Flammable: Do not use near heat, flame, or while smoking.

When using this product

- keep out of eyes. Rinse with water to remove.
- Do not puncture or incinerate. Contents under pressure. Do no store at temperatures above 120F.

Stop use and ask a doctor if

- condition worsens or does not improve within 7 days.

- symptoms persist for more than 7 days or clear up and occur again with in a few days.

Keep out of reach of children

If swallowed, get medical help or contact a Poison Control Center right away.

Directions

- shake well before use.
- adults and children 2 years of age and older: apply to affected area not more than 3 to 4 times daily.
- children under 2 years of age: ask a doctor.

Inactive ingredients

Avena Sativa (Oat) Meal Extract,
Camphor, Citric Acid, Diazolidinyl Urea, Fragrance, Glycerin,
Hydroxypropyl Methylcellulose, Methylparaben, Polysorbate 40,
Propylene Glycol, Propylparaben, SD Alcohol 38-B, Sodium Citrate, Water.
CLEAR SKIN PROTECTANT
Pramoxine HCl 1% - Topical Analgesic
Zinc Acetate 0.1% - Skin Protectant
Drying Action PLUS Itch Relief
Continuous Spray
Relieves Pain And Itch
Associated Wit